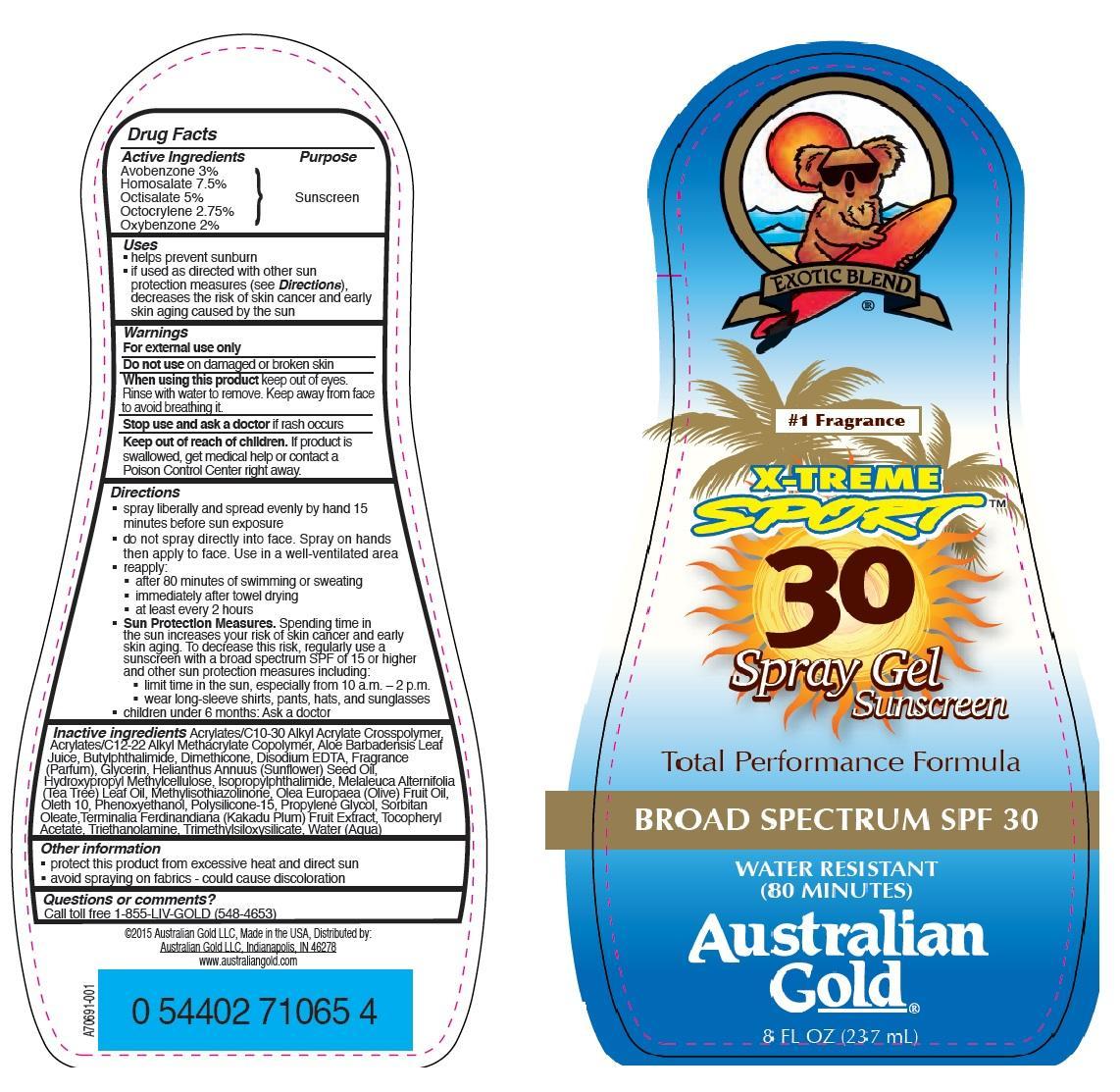 DRUG LABEL: Australian Gold
NDC: 58443-0150 | Form: GEL
Manufacturer: Prime Enterprises, Inc.
Category: otc | Type: HUMAN OTC DRUG LABEL
Date: 20200117

ACTIVE INGREDIENTS: AVOBENZONE 29.4 mg/1 mL; HOMOSALATE 73.5 mg/1 mL; OCTISALATE 49 mg/1 mL; OCTOCRYLENE 26.95 mg/1 mL; OXYBENZONE 19.6 mg/1 mL
INACTIVE INGREDIENTS: C10-30 CHOLESTEROL/LANOSTEROL ESTERS; BUTYL ACRYLATE/C16-C20 ALKYL METHACRYLATE/METHACRYLIC ACID/METHYL METHACRYLATE COPOLYMER; ALOE VERA LEAF; N-BUTYLPHTHALIMIDE; ISOPROPYLPHTHALIMIDE; DIMETHICONE; TRIMETHYLSILOXYSILICATE (M/Q 0.6-0.8); EDETATE DISODIUM; SUNFLOWER OIL; HYPROMELLOSES; MELALEUCA ALTERNIFOLIA LEAF; METHYLISOTHIAZOLINONE; OLIVE OIL; OLETH-10; PHENOXYETHANOL; POLYSILICONE-15; PROPYLENE GLYCOL; SORBITAN MONOOLEATE; .ALPHA.-TOCOPHEROL ACETATE; TROLAMINE; WATER; GLYCERIN; KAKADU PLUM

Active ingredients

Avobenzone 3 %, Homosalate 7.5 %, Octisalate 5 %, Octocrylene 2.75 %, and Oxybenzone 2 %

Purpose

Sunscreen

Uses

- helps prevent sunburn
- if used as directed with other sun protection measures (see Directions), decreases the risk of skin cancer and early skin aging caused by the sun

Warnings

OTHER SAFETY INFORMATION

For external use only

Do not use on damaged or broken skin.

When using this product keep out of eyes. Rinse with water to remove. Keep away from face to avoid breathing it.

Stop use and ask a doctor if rash occurs.

Keep out of reach of children. If product is swallowed, get medical help or contact a Poison Control Center right away.

Directions

- spray liberally and spread evenly 15 minutes before sun exposure
- do not spray directly into face. Use in a well-ventilated area
- reapply:
  - after 80 minutes of swimming or sweating
  - immediately after towel drying
  - at least every 2 hours
- Sun Protection Measures. Spending time in the sun increases your risk of skin cancer and early skin aging. To decrease this risk, regularly use a sunscreen with broad spectrum SPF of 15 or higher and other sun protection measures including:
  - limit time in the sun, especially from 10 a.m. – 2 p.m.
  - wear long-sleeve, shirts, pants, hats, and sunglasses
- Children under 6 months: Ask a doctor

Inactive Ingredients

Acrylates/C10-30 Alkyl Acrylate Crosspolymer, Acrylates/C12-22 Alkyl Methacrylate Copolymer, Aloe Barbadensis Leaf Juice, Butylphthalimide, Dimethicone, Disodium EDTA, Fragrance (Parfum), Glycerin, Helianthus Annuus (Sunflower) Seed Oil, Hydroxypropyl Methylcellulose, Isopropylphthalimide, Melaleuca Alternifolia (Tea Tree) Leaf Oil, Methylisothiazolinone, Olea Europaea (Olive) Fruit Oil, Oleth-10, Phenoxyethanol, Polysilicone-15, Propylene Glycol, Sorbitan Oleate, Terminalia Ferdinandiaria (Kakadum Plum) Fruit Extract, Tocopheryl Acetate, Triethanolamine, Trimethylsiloxysilicate, Water (Aqua)

Other information

- protect this product from excesive heat and direct sun
- avoid spraying on fabrics - could cause discoloration

Questions or Comments?

Call toll free 1-855-LIV-GOLD (548-4653)

PRINCIPAL DISPLAY PANEL - 237 mL Bottle Label

EXOTIC BLEND

#1 Fragrance

X-TREME

SPORT

30

Spray Gel

Sunscreen

Total Performance Formula

BROAD SPECTRUM SPF 30

WATER RESISTANT

(80 MINUTES)

Australian

Gold

8 FL OZ (237 mL)